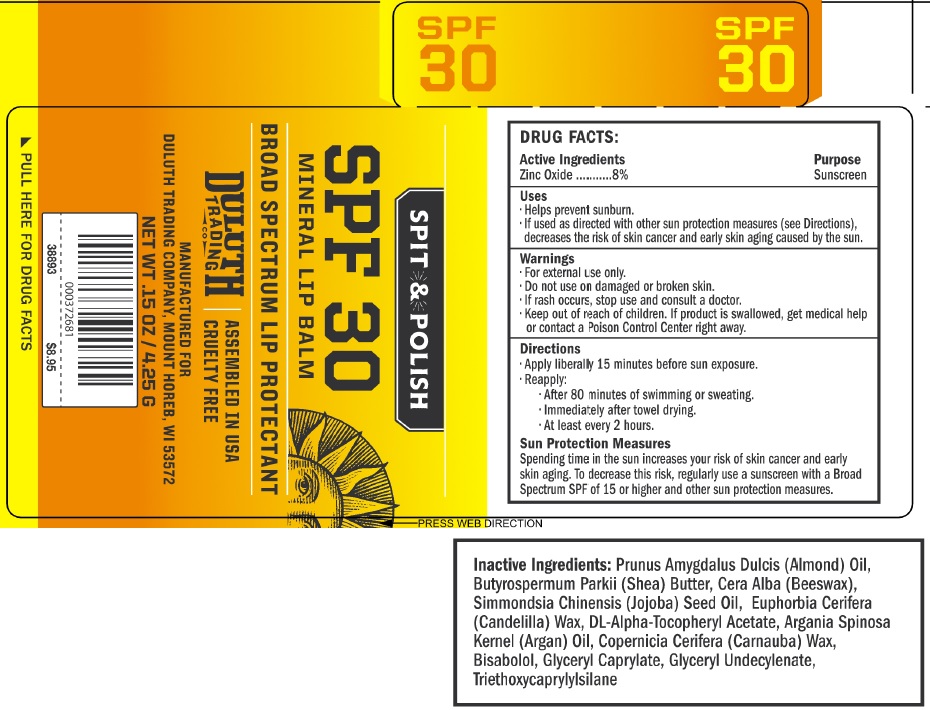 DRUG LABEL: Spit and Polish Mineral Lip Balm Broad Spectrum Lip Protectant SPF 30
NDC: 80325-002 | Form: STICK
Manufacturer: Naturally Uncommon, LLC
Category: otc | Type: HUMAN OTC DRUG LABEL
Date: 20231109

ACTIVE INGREDIENTS: ZINC OXIDE 80 mg/1 g
INACTIVE INGREDIENTS: ALMOND; SHEA BUTTER; YELLOW WAX; JOJOBA OIL; CANDELILLA WAX; .ALPHA.-TOCOPHEROL ACETATE, DL-; ARGAN OIL; CARNAUBA WAX; LEVOMENOL; GLYCERYL MONOCAPRYLATE; GLYCERYL 1-UNDECYLENATE; TRIETHOXYCAPRYLYLSILANE

Spit & Polish Mineral Lip Balm, Broad Spectrum Lip Protectant, SPF 30

Active Ingredients

Zinc Oxide 8%

Purpose

Sunscreen

Uses

- Helps prevent sunburn.
- If used as directed with other sun protection measures (see Directions), decreases the risk of skin cancer and early skin aging caused by the sun.

Warnings:

For external use only.

Do not use

- on damaged or broken skin.
- If rash occurs,

Keep out of reach of children.

- If product is swallowed, get medical help or contact a Poison Control Center right away.

Directions:

- Apply liberally 15 minutes before sun exposure.
- Reapply:
- After 80 minutes of swimming or sweating.
- Immediately after towel drying.
- At least every 2 hours.

Sun protection measures

Spending time in the sun increases your risk of skin cancer and early skin aging. To decrease the risk, regularly use a sunscreen with a Broad Spectrum SPF of 15 or higher and other sun protection measures.

INACTIVE INGREDIENTS:

Prunus Amygdalus Dulcis (Almond) Oil, Butyrospermum Parkii (Shea) Butter, Cera Alba (Beeswax), Simmondsia Chinensis (Jojoba) Seed Oil, Euphorbia Cerifera (Candelilla) Wax, DL-Alpha-Tocopheryl Acetate, Argania Spinosa Kernel (Argan) Oil, Copernicia Cerifera (Carnauba) Wax, Bisabolol, Glyceryl Caprylate, Glyceryl Undecylenate, Triethoxycaprylylsilane